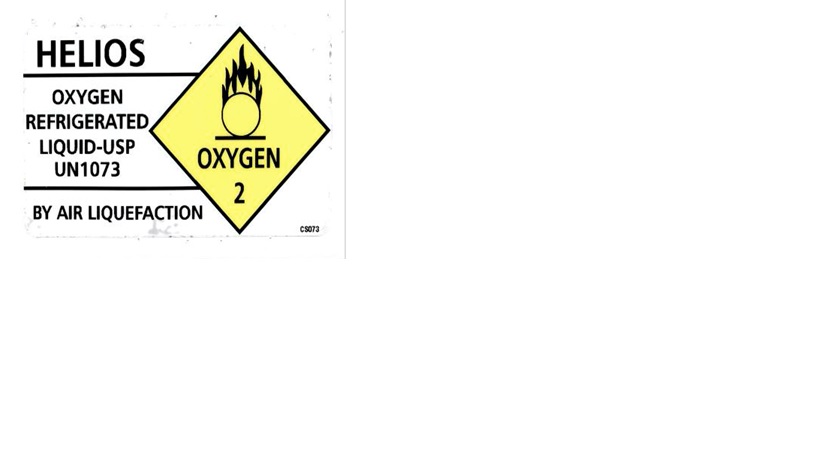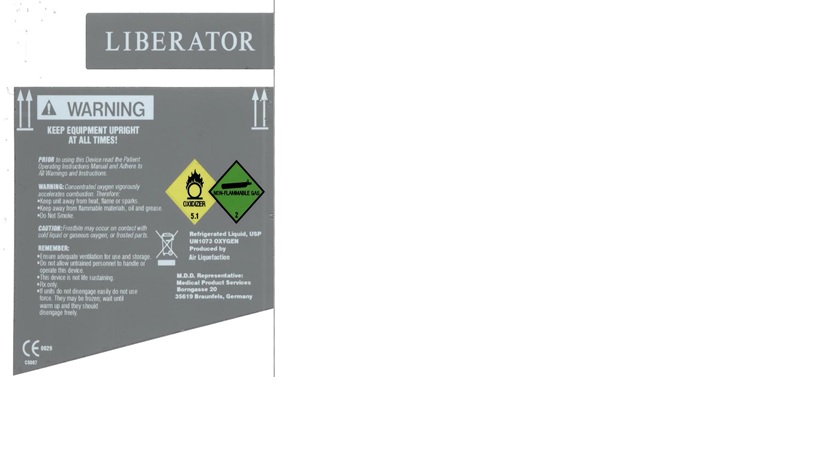 DRUG LABEL: Oxygen
NDC: 59714-012 | Form: GAS
Manufacturer: Airway Oxygen, Inc.
Category: prescription | Type: HUMAN PRESCRIPTION DRUG LABEL
Date: 20191018

ACTIVE INGREDIENTS: OXYGEN 991 mL/1 L

oxygen

PACKAGE LABEL

HELIOS
OXYGEN REFRIGERATED LIQUID-USP
UN1073
BY AIR LIQUEFACTION

PACKAGE LABEL

LIBERATOR
WARNING
KEEP EQUIPMENT UPRIGHT AT ALL TIMES!
PRIOR to using this Device read the Patient Operating Instructions Manual and Adhere to All Warnings and Instructions.
WARNING: Concentrated oxygen vigorously accelerates combustion. Therefore:
Keep unit away from heat, flame or sparks.
Keep away from flammable materials, oil and grease.
Do Not Smoke.
CAUTION: Frostbite may occur on contact with cold liquid or gaseous oxygen, or frosted parts.
REMEMBER:
Ensure adequate ventilation for use and storage.
Do not allow untrained personnel to handle or operate this device.
This device is not life sustaining.
Rx only.
If units do not disengage easily do not use force. They may be frozen; wait until warm up and they should disengage freely.
Refrigerated Liquid, USP
UN073 OXYGEN
Produced by Air Liquefaction
M.D.D. Representative:
Medical Product Services
Borngasse 20
35619 Braunfels, Germany